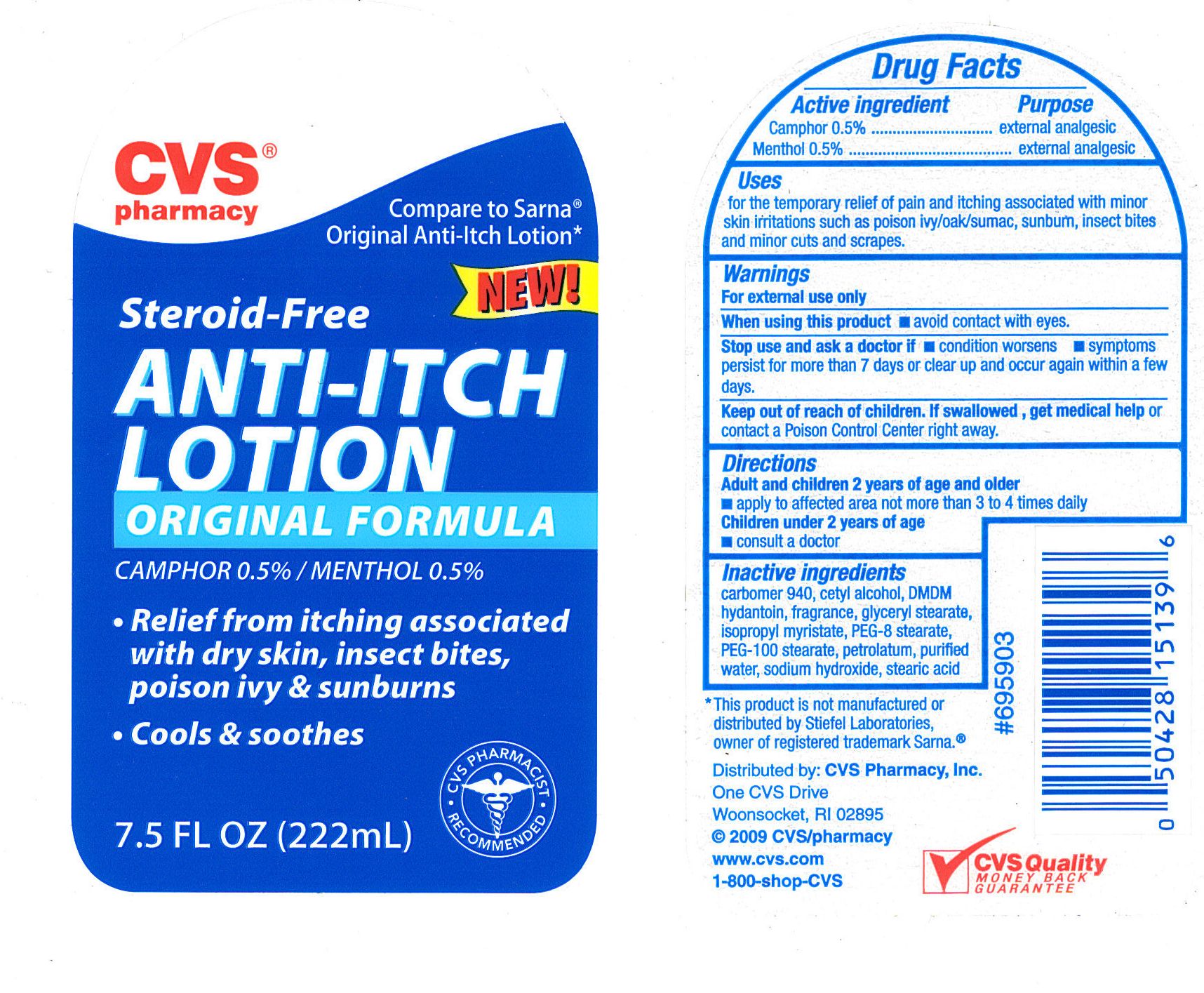 DRUG LABEL: CVS ANTI ITCH
NDC: 59779-713 | Form: LOTION
Manufacturer: CVS
Category: otc | Type: HUMAN OTC DRUG LABEL
Date: 20100708

ACTIVE INGREDIENTS: CAMPHOR (SYNTHETIC) 5 mg/1 mL; MENTHOL 5 mg/1 mL
INACTIVE INGREDIENTS: WATER; CARBOMER HOMOPOLYMER TYPE C; ISOPROPYL MYRISTATE; GLYCERYL MONOSTEARATE; STEARIC ACID; CETYL ALCOHOL; PETROLATUM; DIMETHICONE; POLYETHYLENE GLYCOL 400; DMDM HYDANTOIN; SODIUM HYDROXIDE; POLYOXYL 100 STEARATE

drug facts

Active ingredient Purpose
Camphor 0.5%......................................external analgesic
Menthol 0.5%....................................... external analgesic

Uses
for the temporary relief of pain and itching associated with minor skin irritations such as
poison ivy/oak/sumac, sunburn, insect bites and minor cuts and scrapes.

Keep out of reach of children. If swallowed, get
medical help or contact a Poison Control Center right away.

Uses
for the temporary relief of pain and itching associated with minor skin irritations such as
poison ivy/oak/sumac, sunburn, insect bites and minor cuts and scrapes.

Warnings
For external use only
When using this product - avoid contact with the eyes.
Stop use and ask a doctor if
- condition worsens - symptoms persist for more than 7 days or clear up and
occur again within a few days.
Keep out of reach of children. If swallowed, get
medical help or contact a Poison Control Center right away.

Directions
- Adults and children 2 years of age and older:
- apply to the affected area not more than 3 to 4 times daily.
Children under 2 years of age
- consult a doctor.

Inactive Ingredients
carbomer 940, cetyl alcohol, DMDM hydantion, fragrance, glyceryl stearate,
isopropyl myristate, PEG-8 stearate, PEG-100 stearate, petrolatum, purified water,
sodium hydroxide, stearic acid